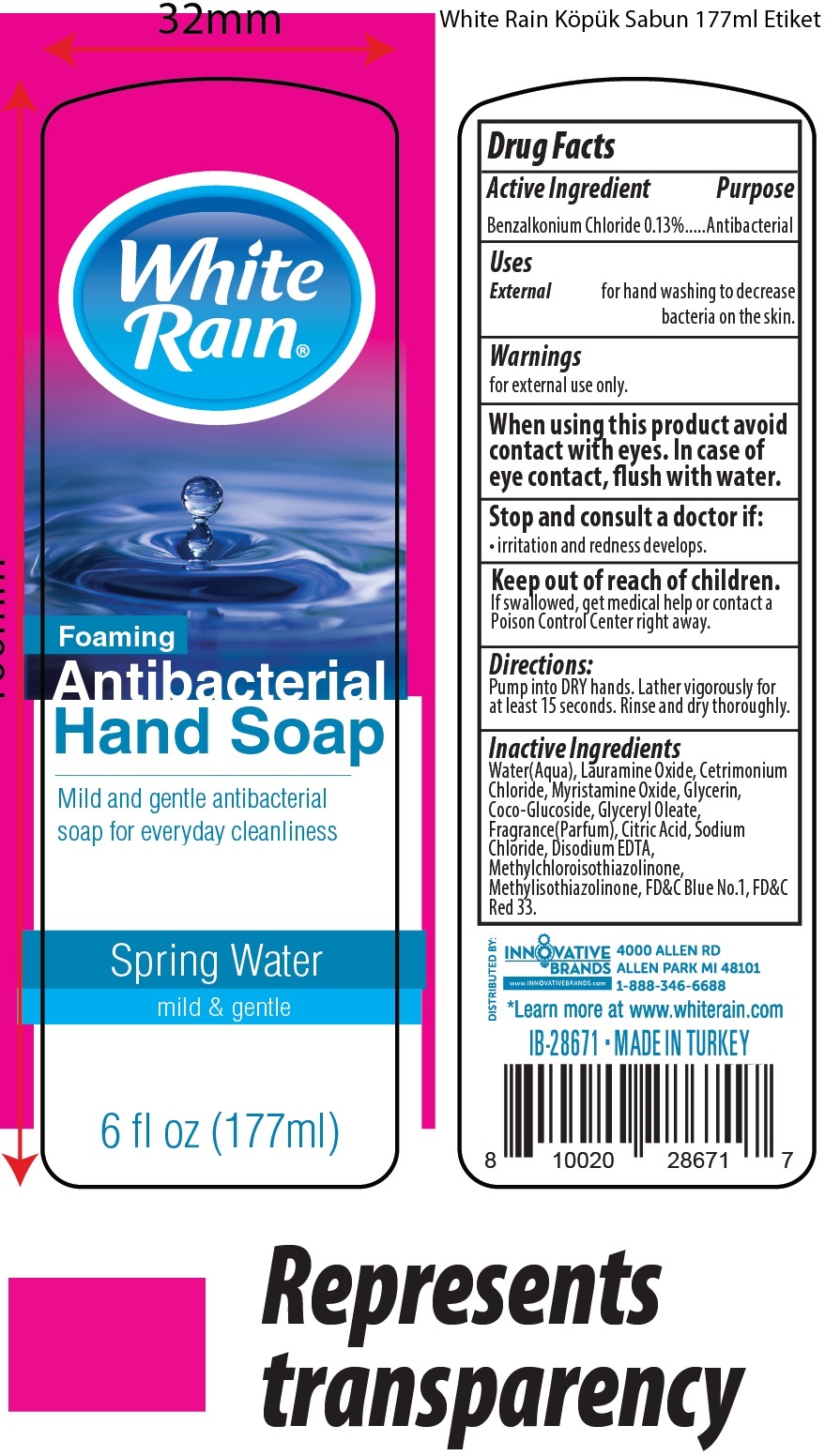 DRUG LABEL: White Rain Foaming Antibacterial Hand Spring Water
NDC: 52862-615 | Form: LIQUID
Manufacturer: International Wholesale, Inc.
Category: otc | Type: HUMAN OTC DRUG LABEL
Date: 20231116

ACTIVE INGREDIENTS: BENZALKONIUM CHLORIDE 1.3 mg/1 mL
INACTIVE INGREDIENTS: LAURAMINE OXIDE; CETRIMONIUM CHLORIDE; MYRISTAMINE OXIDE; WATER; GLYCERIN; COCO GLUCOSIDE; GLYCERYL OLEATE; CITRIC ACID MONOHYDRATE; SODIUM CHLORIDE; EDETATE DISODIUM ANHYDROUS; METHYLCHLOROISOTHIAZOLINONE; METHYLISOTHIAZOLINONE; FD&C BLUE NO. 1

White Rain Foaming Antibacterial Hand Soap Spring Water

Active Ingredient

Benzalkonium Chloride 0.13%

Purpose

Antibacterial

Uses

External

for hand washing to decrease bacteria on the skin.

Warnings

for external use only.

When using this product

avoid contact with eyes. In case of eye contact, flush with water.

Stop use and consult a doctor if:

irritation and redness develops.

Keep out of reach of children.

If swallowed, get medical help or contact a Poison Control Center right away.

Directions:

Pump into DRY hands. Lather vigorously for at least 15 seconds. Rinse and dry thoroughly.

Inactive Ingredients

Water(Aqua), Lauramine Oxide, Cetrimonium Chloride, Myristamine Oxide, Glycerin, Coco-Glucoside, Glyceryl Oleate, Fragrance(Parfum), Citric Acid, Sodium Chloride, Disodium EDTA, Methylchloroisothiazolinone, Methylisothiazolinone, FD&C Blue No.1, FD&C Red 33.